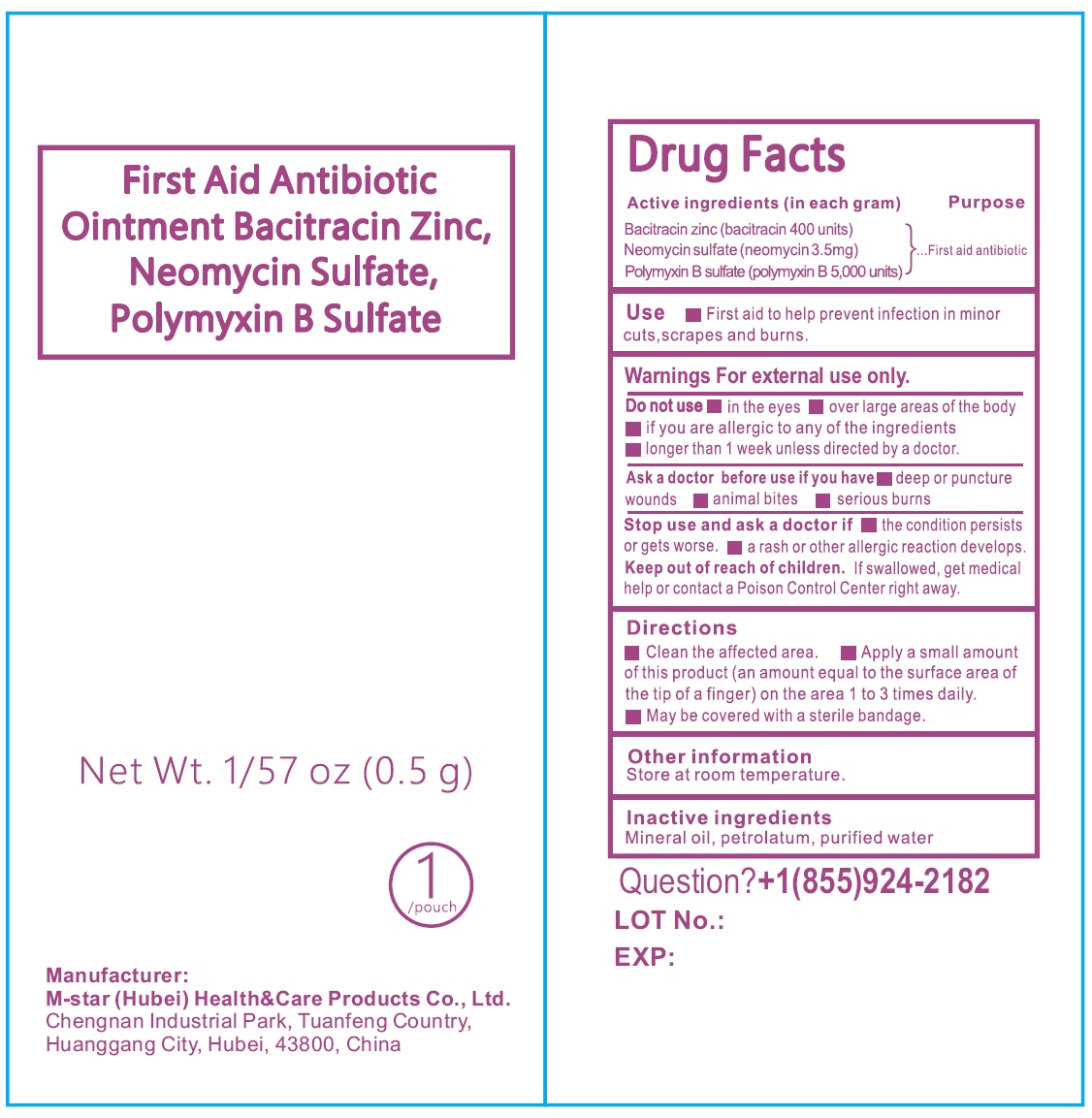 DRUG LABEL: First Aid Antibiotic Bacitracin Zinc Neomycin Sulfate Polymyxin B Sulfate
NDC: 84219-001 | Form: GEL
Manufacturer: M-star (Hubei) Health&Care Products Co., Ltd.
Category: otc | Type: HUMAN OTC DRUG LABEL
Date: 20240401

ACTIVE INGREDIENTS: BACITRACIN ZINC 400 U/1 g; NEOMYCIN SULFATE 3.5 mg/1 g; POLYMYXIN B SULFATE 5000 U/1 g
INACTIVE INGREDIENTS: MINERAL OIL; PETROLATUM; WATER

First Aid Antibiotic Ointment Bacitracin Zinc, Neomycin Sulfate, Polymyxin B Sulfate

Active ingredients (in each gram)

Bacitracin zinc (bacitracin 400 units)

Neomycin sulfate (neomycin 3.5mg)

Polymyxin B sulfate (polymyxin B 5,000 units)

Purpose

First aid antibiotic

Use

- First aid to help prevent infection in minor cuts,scrapes and burns.

Warnings:

For external use only.

Do not use

- in the eyes
- over large areas of the body
- if you are allergic to any of the ingredients
- longer than 1 week unless directed by a doctor.

Ask a doctor before use if you have

- deep or puncture wounds
- animal bites
- serious burns

Stop use and ask a doctor if

- the condition persists or gets worse.
- a rash or other allergic reaction develops.

Keep out of reach of children.

If swallowed, get medical help or contact a Poison Control Center right away.

Directions:

- clean the affected area.
- Apply a small amount of this product (an amount equal to the surface area of the tip of a finger) on the area 1 to 3 times daily.
- May be covered with a sterile bandage.

Other information:

Store at room temperature

Inactive ingredient:

Mineral oil, petrolatum, purified water

Question?

+1(855)924-2182